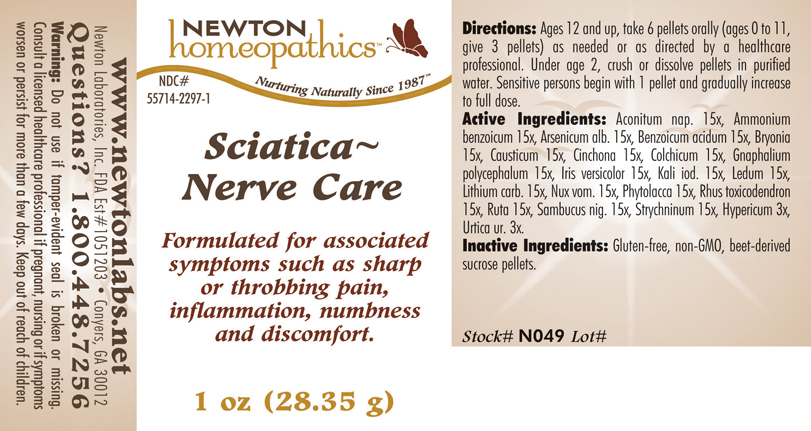 DRUG LABEL: Sciatica - Nerve Care 
NDC: 55714-2297 | Form: PELLET
Manufacturer: Newton Laboratories, Inc.
Category: homeopathic | Type: HUMAN OTC DRUG LABEL
Date: 20110301

ACTIVE INGREDIENTS: Aconitum Napellus 15 [hp_X]/1 g; Ammonium Benzoate 15 [hp_X]/1 g; Arsenic Trioxide 15 [hp_X]/1 g; Benzoic Acid 15 [hp_X]/1 g; Bryonia Alba Root 15 [hp_X]/1 g; Causticum 15 [hp_X]/1 g; Cinchona Officinalis Bark 15 [hp_X]/1 g; Colchicum Autumnale Bulb 15 [hp_X]/1 g; Pseudognaphalium Obtusifolium 15 [hp_X]/1 g; Iris Versicolor Root 15 [hp_X]/1 g; Potassium Iodide 15 [hp_X]/1 g; Ledum Palustre Twig 15 [hp_X]/1 g; Lithium Carbonate 15 [hp_X]/1 g; Strychnos Nux-vomica Seed 15 [hp_X]/1 g; Phytolacca Americana Root 15 [hp_X]/1 g; Toxicodendron Pubescens Leaf 15 [hp_X]/1 g; Ruta Graveolens Flowering Top 15 [hp_X]/1 g; Sambucus Nigra Flowering Top 15 [hp_X]/1 g; Strychnine 15 [hp_X]/1 g; Hypericum Perforatum 3 [hp_X]/1 g; Urtica Urens 3 [hp_X]/1 g
INACTIVE INGREDIENTS: Sucrose

Sciatica - Nerve Care

INDICATIONS & USAGE SECTION

Sciatica - Nerve Care Formulated for associated symptoms such as sharp or throbbing pain, inflammation, numbness and discomfort.

DOSAGE & ADMINISTRATION SECTION

Directions: Ages 12 and up, take 6 pellets orally (ages 0 to 11, give 3 pellets) as needed or as directed by a healthcare professional. Under age 2, crush or dissolve pellets in purified water. Sensitive persons begin with 1 pellet and gradually increase to full dose.

OTC - ACTIVE INGREDIENT SECTION

Aconitum nap. 15x, Ammonium benzoicum 15x, Arsenicum alb. 15x, Benzoicum acidum 15x, Bryonia15x, Causticum 15x, Cinchona 15x, Colchicum 15x, Gnaphalium polycephalum 15x, Iris versicolor 15x, Kali iod. 15x, Ledum 15x, Lithium carb. 15x, Nux vom. 15x, Phytolacca 15x, Rhus toxicodendron 15x, Ruta 15x, Sambucus nig. 15x, Strychninum 15x, Hypericum 3x, Urtica ur. 3x.

OTC - PURPOSE SECTION

Formulated for associated symptoms such as sharp or throbbing pain, inflammation, numbness and discomfort.

INACTIVE INGREDIENT SECTION

Inactive Ingredients: Gluten-free, non-GMO, beet-derived sucrose pellets.

QUESTIONS SECTION

www.newtonlabs.net Newton Laboratories, Inc. FDA Est # 1051203 - Conyers, GA 30012
Questions? 1.800.448.7256

WARNINGS SECTION

Warning: Do not use if tamper - evident seal is broken or missing. Consult a licensed healthcare professional if pregnant, nursing or if symptoms worsen or persist for more than a few days. Keep out of reach of children.

OTC - PREGNANCY OR BREAST FEEDING SECTION

Consult a licensed healthcare professional if pregnant, nursing or if symptoms worsen or persist for more than a few days.

OTC - KEEP OUT OF REACH OF CHILDREN SECTION

Keep out of reach of children.